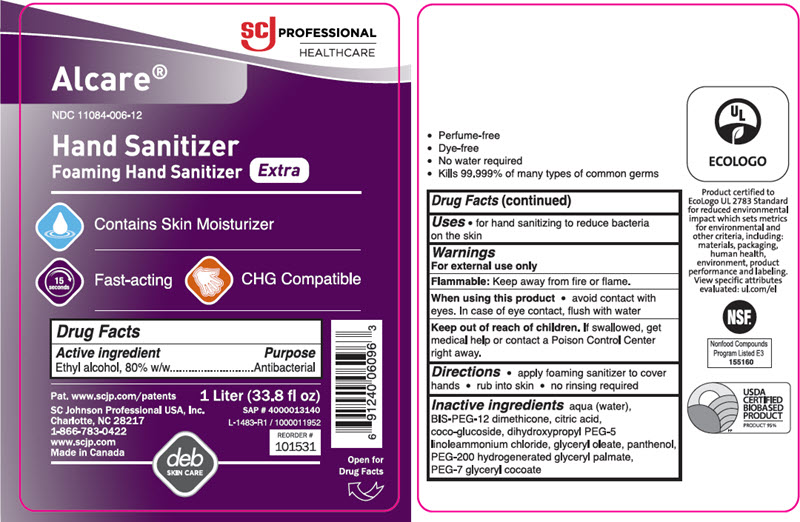 DRUG LABEL: Alcare Extra Hand Sanitizer
NDC: 11084-006 | Form: SOLUTION
Manufacturer: SC Johnson Professional USA, Inc.
Category: otc | Type: HUMAN OTC DRUG LABEL
Date: 20251006

ACTIVE INGREDIENTS: ALCOHOL 80 mL/100 mL
INACTIVE INGREDIENTS: WATER; BIS-PEG-12 DIMETHICONE (500 MPA.S); ANHYDROUS CITRIC ACID; COCO-GLUCOSIDE; DIHYDROXYPROPYL PEG-5 LINOLEAMMONIUM CHLORIDE; GLYCERYL OLEATE; PANTHENOL; PEG-200 HYDROGENATED GLYCERYL PALMATE; PEG-7 GLYCERYL COCOATE

Drug Facts

Active ingredient

ETHYL ALCOHOL, 80% w/w

Purpose

Antibacterial

Uses

for hand sanitizing to reduce bacteria on the skin

Warnings

Flammable:

Keep away from fire or flame.

When using this product

avoid contact with eyes. In case of eye contact, flush with water.

Keep out of reach of children.

If swallowed, get medical help or contact a Poison Control Center right away.

Directions

apply foaming sanitizer to cover hands

rub into skin

no rinsing required

Inactive ingredients

AQUA (WATER), BIS-PEG-12 DIMETHICONE, CITRIC ACID, COCO-GLUCOSIDE, DIHYDROXYPROPYL PEG-5 LINOLEAMMONIUM CHLORIDE, GLYCERYL OLEATE, PANTHENOL, PEG-200 HYDROGENATED GLYCERYL PALMITATE, PEG-7 GLYCERYL COCOATE

PRINCIPAL DISPLAY PANEL - 1 Liter Bottle Label

SCJ PROFESSIONAL
HEALTHCARE

Alcare®

NDC 11084-006-12

Hand Sanitizer
Foaming Hand Sanitizer Extra

Contains Skin Moisturizer

15
seconds

Fast-acting

CHG Compatible

Pat.www.scjp.com/patents
SC Johnson Professional USA, Inc.
Charlotte, NC 28217
1-866-783-0422
www.scjp.com
Made in Canada

1 Liter (33.8 fl oz)
SAP # 4000013140
L-1483-R1 / 1000011952

REORDER #
101531

deb
SKIN CARE

Open for
Drug Facts